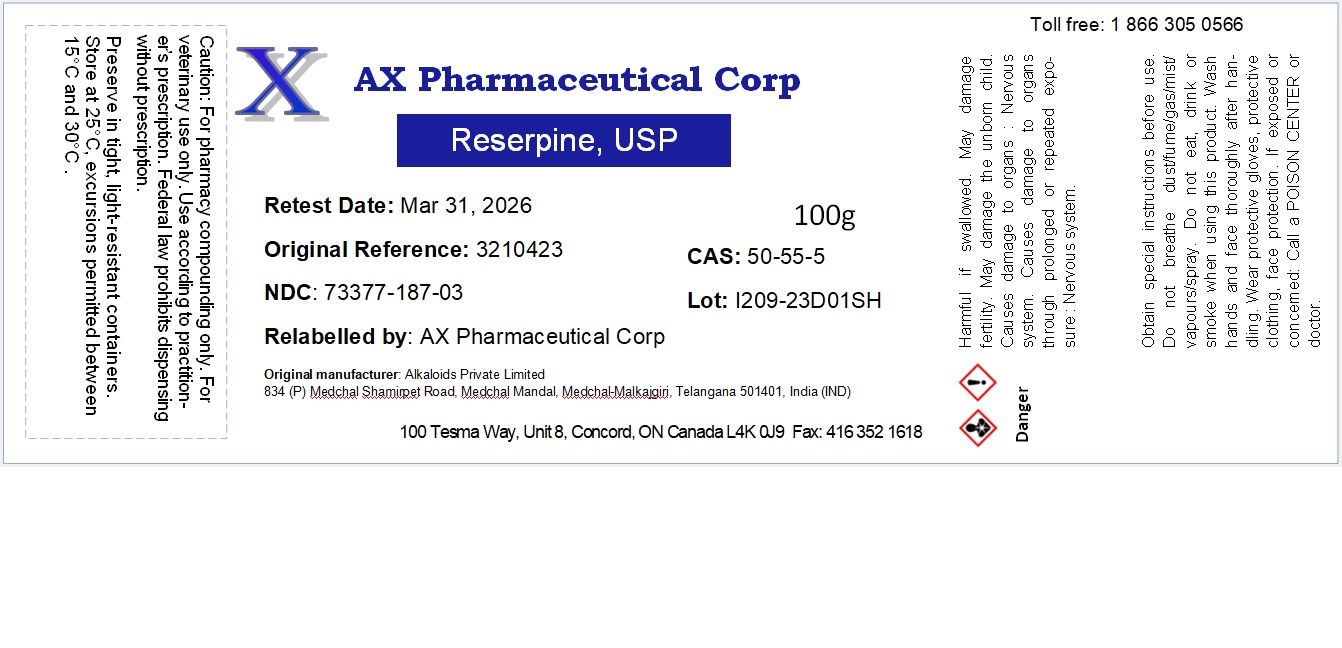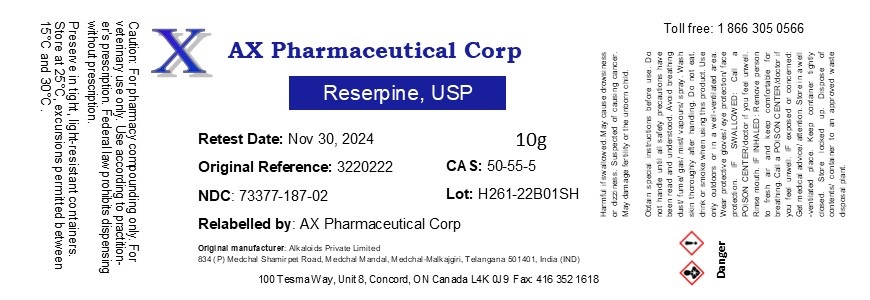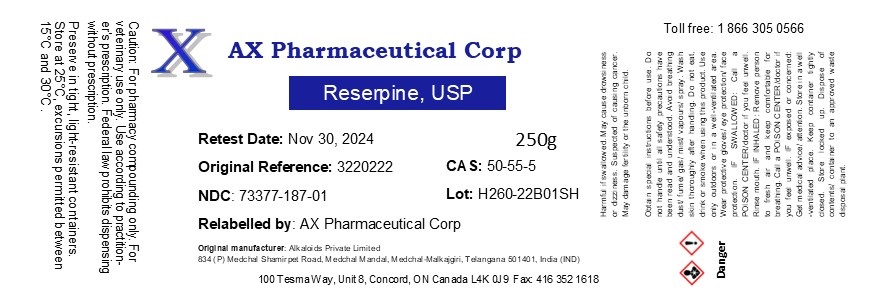 DRUG LABEL: Reserpine
NDC: 73377-187 | Form: POWDER
Manufacturer: AX Pharmaceutical Corp
Category: other | Type: BULK INGREDIENT - ANIMAL DRUG
Date: 20241021

ACTIVE INGREDIENTS: RESERPINE 1 g/1 g

Reserpine